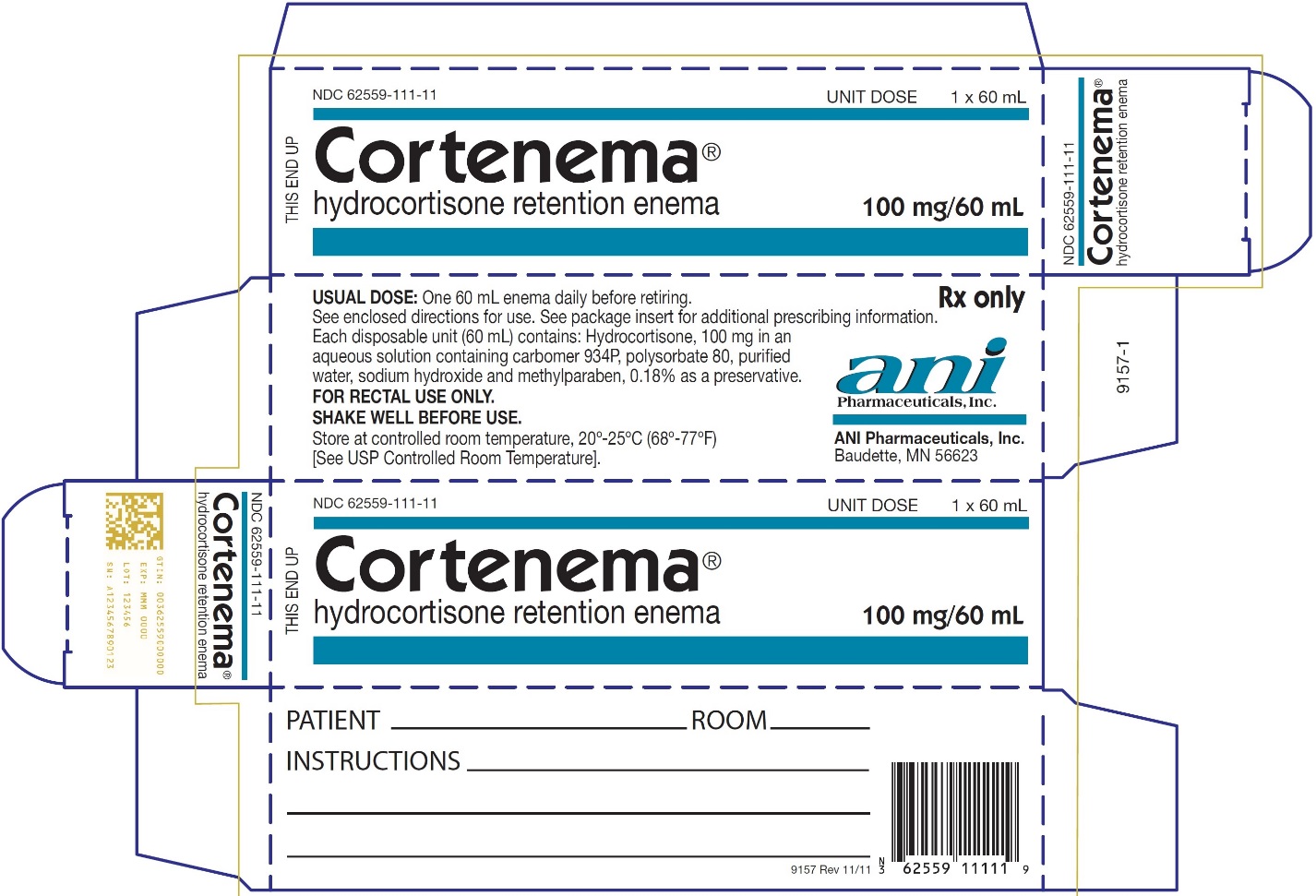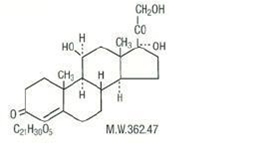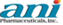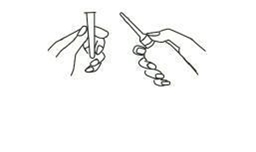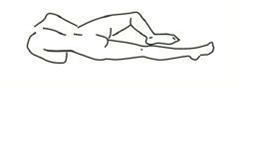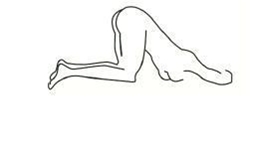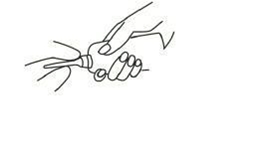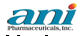 DRUG LABEL: Cortenema
NDC: 62559-111 | Form: ENEMA
Manufacturer: ANI Pharmaceuticals, Inc.
Category: prescription | Type: HUMAN PRESCRIPTION DRUG LABEL
Date: 20220427

ACTIVE INGREDIENTS: HYDROCORTISONE 100 mg/60 mL
INACTIVE INGREDIENTS: CARBOMER HOMOPOLYMER TYPE B (ALLYL PENTAERYTHRITOL OR ALLYL SUCROSE CROSSLINKED); POLYSORBATE 80; WATER; SODIUM HYDROXIDE; METHYLPARABEN

CORTENEMA®
hydrocortisone retention enema
100 mg / 60 mL
DISPOSABLE UNIT FOR RECTAL USE ONLY

DESCRIPTION

Hydrocortisone is a white to practically white, odorless, crystalline powder, very slightly soluble in water. It has the chemical name Pregn-4-ene-3,20-dione,11,17,21-trihydroxy,(11β)-and the following structural formula:

CORTENEMA® is a convenient disposable single-dose hydrocortisone enema designed for ease of self-administration.

Each disposable unit (60 mL) contains: Hydrocortisone, 100 mg in an aqueous solution containing carbomer 934P, polysorbate 80, purified water, sodium hydroxide and methylparaben, 0.18% as a preservative.

CLINICAL PHARMACOLOGY

Hydrocortisone is a naturally occurring glucocorticoid (adrenal corticosteroid), similar to its acetate and sodium hemisuccinate derivatives, is partially absorbed following rectal administration. Absorption studies in ulcerative colitis patients have shown up to 50% absorption of hydrocortisone administered as CORTENEMA® and up to 30% of hydrocortisone acetate administered in an identical vehicle.

CORTENEMA® provides the potent anti-inflammatory effect of hydrocortisone. Because this drug is absorbed from the colon, it acts both topically and systemically. Although rectal hydrocortisone, used as recommended for CORTENEMA®, has a low incidence of reported adverse reactions, prolonged use presumably may cause systemic reactions associated with oral dosage forms.

INDICATIONS AND USAGE

CORTENEMA® is indicated as adjunctive therapy in the treatment of ulcerative colitis, especially distal forms, including ulcerative proctitis, ulcerative proctosigmoiditis, and left-sided ulcerative colitis. It has proved useful also in some cases involving the transverse and ascending colons.

CONTRAINDICATIONS

Systemic fungal infections; and ileocolostomy during the immediate or early post-operative period.

WARNINGS

In severe ulcerative colitis, it is hazardous to delay needed surgery while awaiting response to medical treatment.

Damage to the rectal wall can result from careless or improper insertion of an enema tip.

In patients on corticosteroid therapy subjected to unusual stress, increased dosage of rapidly acting corticosteroids before, during, and after the stressful situation is indicated.

Corticosteroids may mask some signs of infection, and new infections may appear during their use. There may be decreased resistance and inability to localize infection when corticosteroids are used.

Prolonged use of corticosteroids may produce posterior subcapsular cataracts, glaucoma with possible damage to the optic nerves, and may enhance the establishment of secondary ocular infections due to fungi or viruses.

Usage in pregnancy:

Since adequate human reproduction studies have not been done with corticosteroids, the use of these drugs in pregnancy, nursing mothers or women of child-bearing potential requires that the possible benefits of the drug be weighed against the potential hazards to the mother and embryo or fetus. Neonates born of mothers who have received substantial doses of corticosteroid during pregnancy should be carefully observed for signs of hypoadrenalism.

Average and large doses of hydrocortisone or cortisone can cause elevation of blood pressure, salt and water retention, and increased excretion of potassium. These effects are less likely to occur with the synthetic derivatives except when used in large doses. Dietary salt restriction and potassium supplementation may be necessary. All corticosteroids increase calcium excretion.

While on corticosteroid therapy patients should not be vaccinated against smallpox. Other immunization procedures should not be undertaken in patients who are on corticosteroids, especially on high dose, because of possible hazards of neurological complications and a lack of antibody response.

Persons who are on drugs which suppress the immune system are more susceptible to infections than healthy individuals. Chicken pox and measles, for example, can have a more serious or even fatal course in non-immune pediatric patients or adults on corticosteroids. In such pediatric patients or adults who have not had these diseases, particular care should be taken to avoid exposure. How the dose, route and duration of corticosteroid administration affects the risk of developing a disseminated infection is not known. The contribution of the underlying disease and/or prior corticosteroid treatment to the risk is also not known. If exposed to chicken pox, prophylaxis with varicella zoster immune globulin (VZIG) may be indicated. If exposed to measles, prophylaxis with pooled intramuscular immunoglobulin (IG) may be indicated. (See the respective package inserts for complete VZIG and IG prescribing information.) If chicken pox develops, treatment with antiviral agents may be considered.

If corticosteroids are indicated in patients with latent tuberculosis or tuberculin reactivity, close observation is necessary as reactivation of the disease may occur. During prolonged corticosteroid therapy, these patients should receive chemoprophylaxis.

PRECAUTIONS

General:

CORTENEMA® hydrocortisone retention enema should be used with caution where there is a probability of impending perforation, abscess or other pyogenic infection; fresh intestinal anastomoses; obstruction; or extensive fistulas and sinus tracts. Use with caution in presence of active or latent peptic ulcer; diverticulitis; renal insufficiency; hypertension; osteoporosis; and myasthenia gravis.

Steroid therapy might impair prognosis in surgery by increasing the hazard of infection. If infection is suspected, appropriate antibiotic therapy must be administered, usually in larger than ordinary doses.

Drug-induced secondary adrenocortical insufficiency may occur with prolonged CORTENEMA® therapy. This is minimized by gradual reduction of dosage. This type of relative insufficiency may persist for months after discontinuation of therapy; therefore, in any situation of stress occurring during that period, hormone therapy should be reinstituted. Since mineralocorticoid secretion may be impaired, salt and/or a mineralocorticoid should be administered concurrently.

There is an enhanced effect of corticosteroids on patients with hypothyroidism and in those with cirrhosis.

Corticosteroid should be used cautiously in patients with ocular herpes simplex because of possible corneal perforation.

The lowest possible dose of corticosteroid should be used to control the conditions under treatment, and when reduction in dosage is possible, the reduction should be gradual.

Psychic derangement may appear when corticosteroids are used, ranging from euphoria, insomnia, mood swings, personality changes, and severe depression, to frank psychotic manifestations. Also, existing emotional instability or psychotic tendencies may be aggravated by corticosteroids.

Aspirin should be used cautiously in conjunction with corticosteroids in hypoprothrombinemia.

Pediatric Use:

Safety and effectiveness in pediatric patients have not been established.

Growth and development of pediatric patients on prolonged corticosteroid therapy should be carefully observed.

Information for Patients:

Persons who are on immunosuppressant doses of corticosteroids should be warned to avoid exposure to chicken pox or measles. Patients should also be advised that if they are exposed, medical advice should be sought without delay.

ADVERSE REACTIONS

Local pain or burning, and rectal bleeding attributed to CORTENEMA® have been reported rarely. Apparent exacerbations or sensitivity reactions also occur rarely. The following adverse reactions should be kept in mind whenever corticosteroids are given by rectal administration.

Fluid and Electrolyte Disturbances: Sodium retention; fluid retention; congestive heart failure in susceptible patients; potassium loss; hypokalemic alkalosis; hypertension. Musculoskeletal: Muscle weakness; steroid myopathy; loss of muscle mass; osteoporosis; vertebral compression fractures; asceptic necrosis of femoral and humeral heads; pathologic fracture of long bones. Gastrointestinal: Peptic ulcer with possible perforation and hemorrhage; pancreatitis; abdominal distention; ulcerative esophagitis. Dermatologic: Impaired wound healing; thin fragile skin; petechiae and ecchymoses; facial erythema; increased sweating; may suppress reactions to skin tests. Neurological: Convulsions; increased intracranial pressure with papilledema (pseudo-tumor cerebri) usually after treatment; vertigo; headache. Endocrine: Menstrual irregularities; development of Cushingoid state; suppression of growth in pediatric patients; secondary adrenocortical and pituitary unresponsiveness, particularly in times of stress, as in trauma, surgery or illness, decreased carbohydrate tolerance; manifestations of latent diabetes requirements for insulin or oral hypoglycemic agents in diabetics. Ophthalmic: Posterior subcapsular cataracts; increased intraocular pressure; glaucoma; exophthalmos. Metabolic: Negative nitrogen balance due to protein catabolism.

DOSAGE AND ADMINISTRATION

The use of CORTENEMA® hydrocortisone retention enema is predicated upon the concomitant use of modern supportive measures such as rational dietary control, sedatives, antidiarrheal agents, antibacterial therapy, blood replacement if necessary, etc.

The usual course of therapy is one CORTENEMA® nightly for 21 days, or until the patient comes into remission both clinically and proctologically. Clinical symptoms usually subside promptly within 3 to 5 days. Improvement in the appearance of the mucosa, as seen by sigmoidoscopic examination, may lag somewhat behind clinical improvement. Difficult cases may require as long as 2 or 3 months of CORTENEMA® treatment. Where the course of therapy extends beyond 21 days, CORTENEMA® should be discontinued gradually by reducing administration to every other night for 2 or 3 weeks.

If clinical or proctologic improvement fails to occur within 2 or 3 weeks after starting CORTENEMA®, discontinue its use.

Symptomatic improvement, evidenced by decreased diarrhea and bleeding; weight gain; improved appetite; lessened fever; and decrease in leukocytosis, may be misleading and should not be used as the sole criterion in judging efficacy. Sigmoidoscopic examination and X-ray visualization are essential for adequate monitoring of ulcerative colitis. Biopsy is useful for differential diagnosis.

Patient instructions for administering CORTENEMA® are enclosed in each box. It is recommended that the patient lie on their left side during administration and for 30 minutes thereafter, so that the fluid will distribute throughout the left colon. Every effort should be made to retain the enema for at least an hour and preferably, all night. This may be facilitated by prior sedation and/or antidiarrheal medication, especially early in therapy when the urge to evacuate is great.

HOW SUPPLIED

CORTENEMA®, hydrocortisone 100 mg retention enema, is supplied as disposable single-dose bottles with lubricated rectal applicator tips, in boxes of seven x 60 mL (NDC 62559-111-07) and boxes of one x 60 mL (NDC 62559-111-11).

Store at controlled room temperature 20° - 25°C (68° - 77°F). [See USP Controlled Room Temperature.]

Rx ONLY

Manufactured by
ANI Pharmaceuticals, Inc.
Baudette, MN 56623

9156 Rev 11/11

Patient Instructions

How to use the retention enema:

Best results are achieved if the bowel is emptied immediately before the enema is given.

1. Preparing the Medication for Administration

a Shake the bottle well to make sure that the suspension is homogeneous.

b Remove the protective sheath from the applicator tip. Hold the bottle at the neck so as not to cause any of the medication to be discharged.

2. Assuming the Correct Body Position

a Best results are obtained by lying on left side with the left leg extended and the right leg flexed forward for balance.

b An alternative to lying on the left side is the “knee-chest” position as shown here.

3. Administering the Retention Enema

a Gently insert the lubricated applicator tip into the rectum, pointed slightly toward the navel (umbilicus).

b Grasp the bottle firmly, then tilt slightly so that the nozzle is aimed toward the back, and squeeze slowly to instill the medication. Steady hand pressure will discharge most of the solution. After administering, withdraw and discard the used unit.

c Remain in position for at least 30 minutes to allow thorough distribution of the medication internally. Retain the enema all night, if possible.

Manufactured by
ANI Pharmaceuticals, Inc.
Baudette, MN 56623

9156 Rev 11/11

PACKAGE/LABEL PRINCIPAL DISPLAY PANEL

Carton Label

Cortenema®
hydrocortisone retention enema, 100 mg/60 mL
NDC 62559-111-11
UNIT DOSE 1 x 60 mL
Rx only